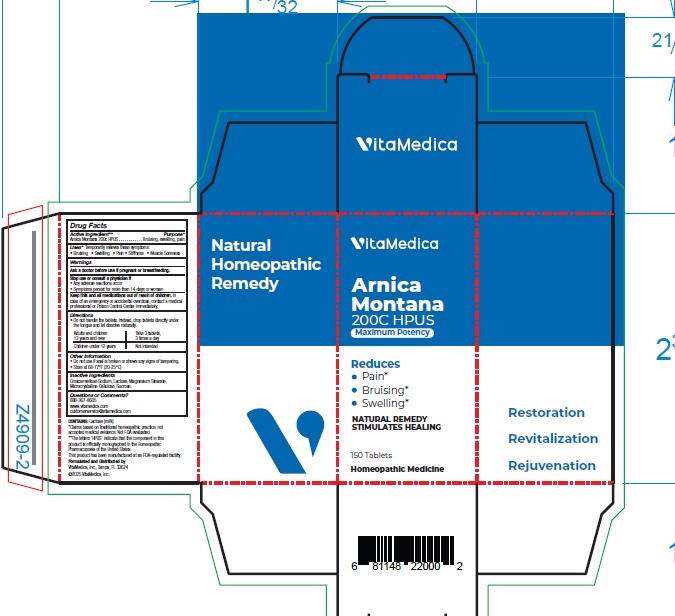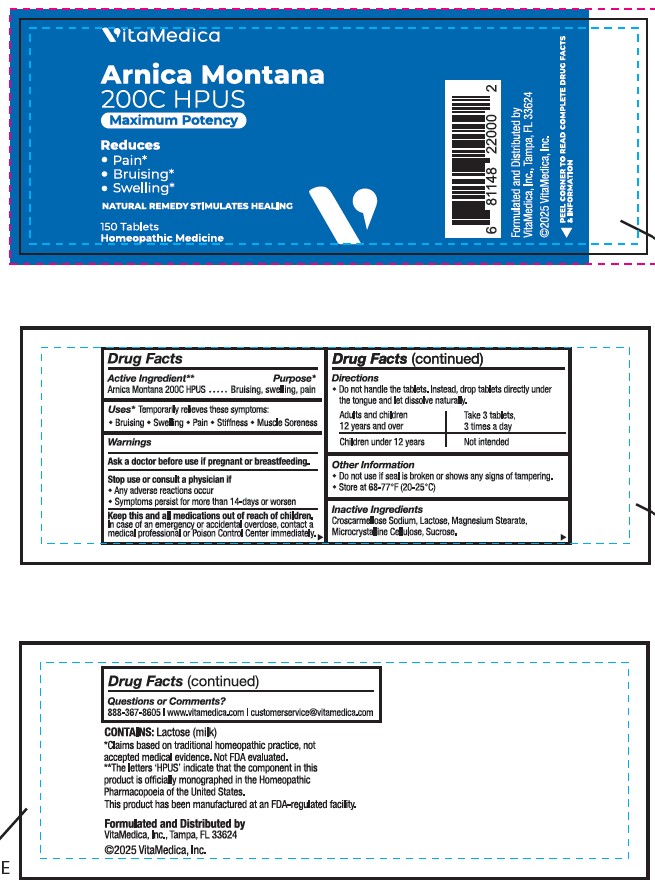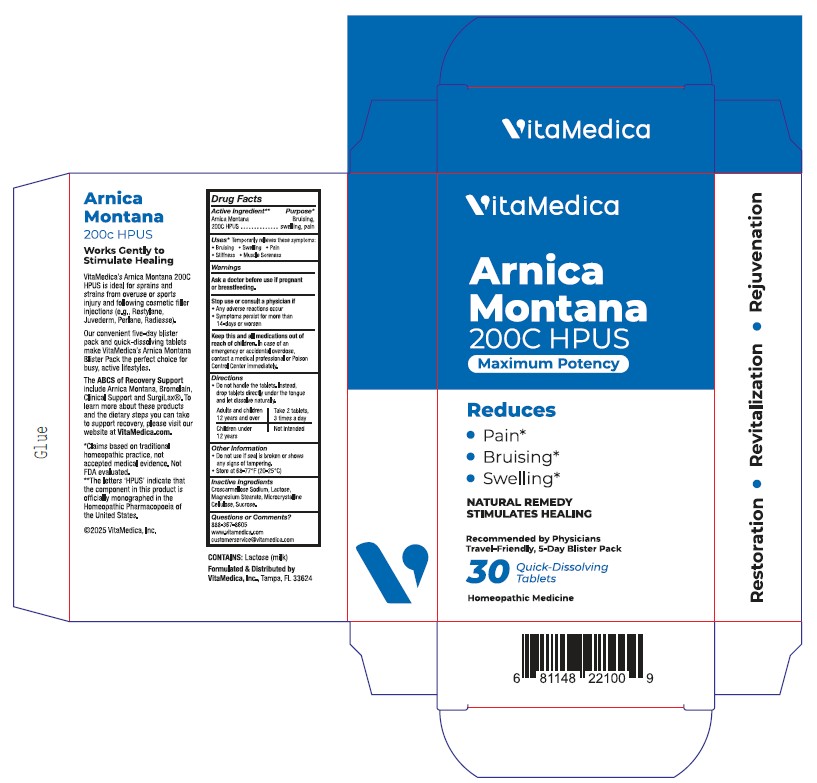 DRUG LABEL: Arnica Montana
NDC: 80004-200 | Form: TABLET
Manufacturer: VITAMEDICA, INC.
Category: homeopathic | Type: HUMAN OTC DRUG LABEL
Date: 20250828

ACTIVE INGREDIENTS: ARNICA MONTANA WHOLE 200 [hp_C]/1 1
INACTIVE INGREDIENTS: CROSCARMELLOSE SODIUM; LACTOSE MONOHYDRATE; MAGNESIUM STEARATE; MICROCRYSTALLINE CELLULOSE; SUCROSE

DRUG FACTS:

ACTIVE INGREDIENT:

Arnica Montana 200C HPUS.**

**The letters 'HPUS' indicate that the component in this product is officially monographed in the Homeopathic Pharmacopoeia of the United States. This product has been manufactured at an FDA-regulated facility.

PURPOSE:

Arnica Montana - Bruising, swelling, pain*

*Claims based on traditional homeopathic practice, not accepted medical evidence. Not FDA evaluated.

USES:

*Temporarily relieves these symptoms:

• Bruising • Swelling • Pain • Stiff • Muscle Soreness

*Claims based on traditional homeopathic practice, not accepted medical evidence. Not FDA evaluated.

WARNINGS:

Ask a doctor before use if pregnant or breastfeeding.

Stop use or consult a physician if

• Any adverse reactions occur

• Symptoms persist for more than 14-days or worsen

Discontinue use if any adverse reactions occur.

Keep this and all medications out of reach of children.

In case of an emergency or accidental overdose, contact a medical professional or Poison Control immediately.

KEEP OUT OF REACH OF CHILDREN:

In case of an emergency or accidental overdose, contact a medical professional or Poison Control immediately.

DIRECTIONS:

• Do not handle the tablets. Instead, drop tablets directly under the tongue and let dissolve naturally.

Adults and children 12 years and over - Take 3 tablets, 3 times a day

Children under 12 years - Not intended

Other Information

• Do not use if seal is broken or shows any signs of tampering.

• Store at 68-77°F (20-25°C)

INACTIVE INGREDIENTS:

Copovidone, Crospovidone, Lactose, Magnesium Stearate, Mannitol, Microcrystalline Cellulose, Silicon Dioxide, and Sorbitol.

QUESTIONS:

Formulated and Distributed by

VitaMedica, Inc.

Tampa, FL 33624

©2024 VitaMedica, Inc.

www.vitamedica.com

888-367-8605

customerservice@vitamedica.com

Label

NDC 80004-200-10

150 Count Bottle

1 Bottle Per Carton

NDC 80004-200-20

30 Blister

1 Blister Carton